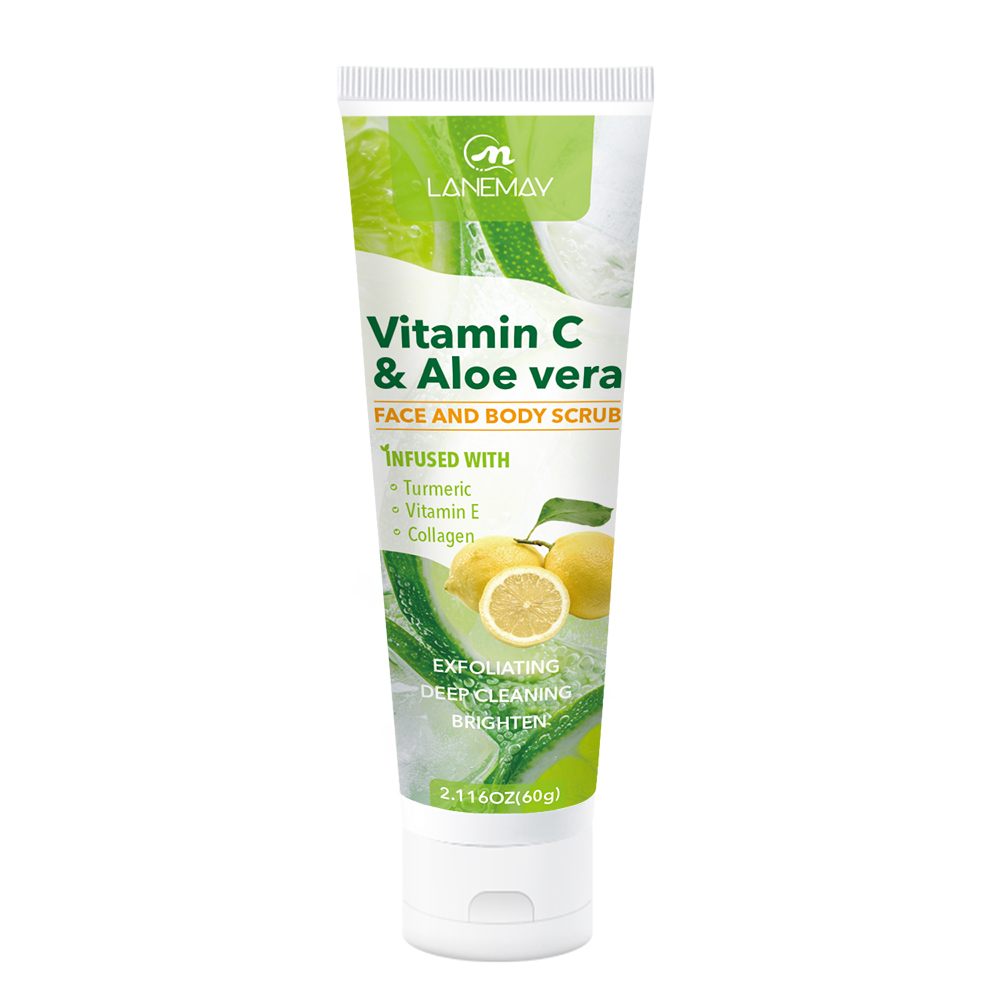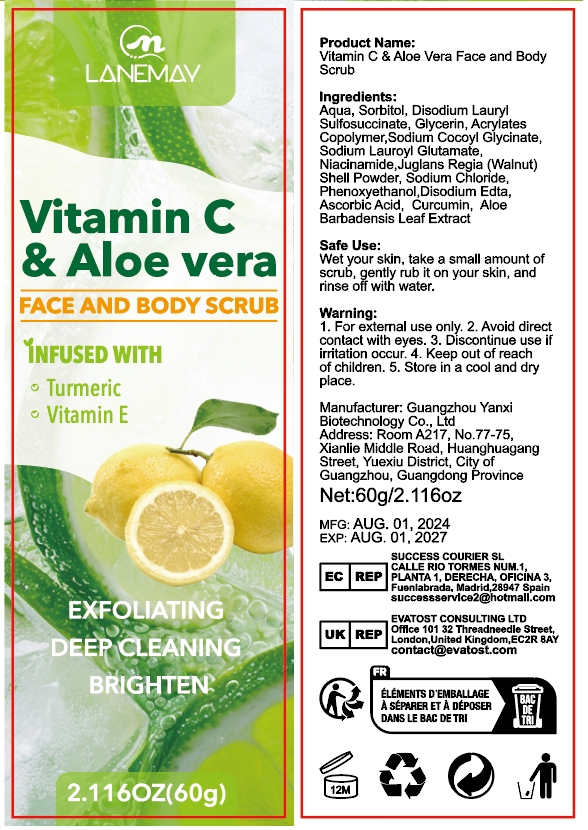 DRUG LABEL: Vitamin C Aloe Vera Face and Body Scrub
NDC: 84025-259 | Form: CREAM
Manufacturer: Guangzhou Yanxi Biotechnology Co., Ltd
Category: otc | Type: HUMAN OTC DRUG LABEL
Date: 20241111

ACTIVE INGREDIENTS: SORBITOL 5 mg/100 g; GLYCERIN 3 mg/100 g
INACTIVE INGREDIENTS: WATER

DOSAGE AND ADMINISTRATION

Vet your skin, take a small amount ot scrub, gently rub it on your skin, and rinse off with water.

WARNINGS

Keep out of children

INACTIVE INGREDIENT

Aqua

INDICATIONS AND USAGE

for daily dace and body care

keep out of children

PURPOSE

wet your skin